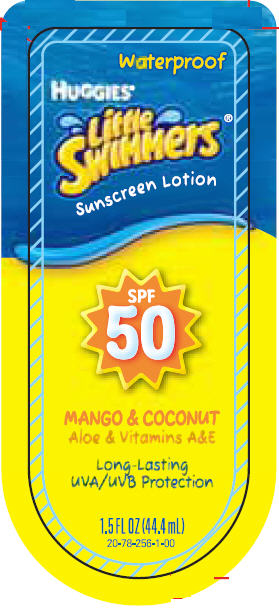 DRUG LABEL: Sunscreen Mango and Coconut
NDC: 55118-600 | Form: LOTION
Manufacturer: Kimberly-Clark Corporation
Category: otc | Type: HUMAN OTC DRUG LABEL
Date: 20100303

ACTIVE INGREDIENTS: Avobenzone 10 mg/1 g; Octinoxate 75 mg/1 g; Octisalate 50 mg/1 g; Octocrylene 8 mg/1 g; Oxybenzone 50 mg/1 g

Huggies®
Little
Swimmers®

Drug Facts

Active ingredients

Avobenzone 1%, Octinoxate 7.5%, Octisalate 5%, Octocrylene 0.8%, Oxybenzone 5%

Purpose

Sunscreen

Uses

- Helps prevent sunburn.
- Higher SPF gives more sunburn protection.
- Retains SPF after 80 minutes of activity in the water or sweating.

Warnings

For external use only.

When using this product, keep out of eyes. Rinse with water to remove.

Stop use and ask a doctor if rash or irritation develops and lasts.

Keep out of reach of children. If swallowed, get medical help or contact a Poison Control Center right away.

Directions

- Apply generously 15 minutes before sun exposure and as needed.
- Reapply as needed or after towel drying, swimming or sweating.
- Ask a doctor before use on children under six months of age.

Other information

Sun alert: Limiting sun exposure, wearing protective clothing, and using sunscreens may reduce the risks of skin aging, skin cancer and other harmful effects of the sun.

Inactive ingredients

Water/Aqua, C12-15 Alkyl Benzoate, Octyldodecyl Neopentanoate, Styrene/Acrylates Copolymer, Aluminum Starch Octenylsuccinate, Glycerin, Cetyl Phosphate, Caprylyl Glycol, Acrylates/C12 -22 Alkyl Methacrylate Copolymer, Dimethicone, Microcrystalline Cellulose, Phenoxyethanol, Acrylates /C10-30 Alkyl Acrylate Crosspolymer, Potassium Hydroxide, 1, 2- Hexanediol, Magnesium Aluminum Silicate, Cellulose Gum, Dimethiconol, Boron Nitride, Disodium EDTA, Aloe Barbadensis Leaf Extract, Cocos Nucifera (Coconut) Fruit Extract, Mangifera Indica (Mango) Fruit Extract, Tropolone, Retinyl Palmitate, Tocopheryl Acetate, Fragrance/Parfum.

Questions?

1-877-546-2273 Mo–Fr, 8 am–4 pm CT. Serious side effects associated with the use of this product may be reported to this number.

Distributed by Kimberly-Clark
Global Sales, LLC, Neenah, WI
54956. Made in the U.S.

PRINCIPAL DISPLAY PANEL 44.4 mL Label

Waterproof

HUGGIES®

Little
Swimmers®

Sunscreen Lotion

SPF
50

MANGO & COCONUT
Aloe & Vitamins A&E

Long-Lasting
UVA/UVB Protection

1.5 FL OZ (44.4 mL)
20-78-256-1-00